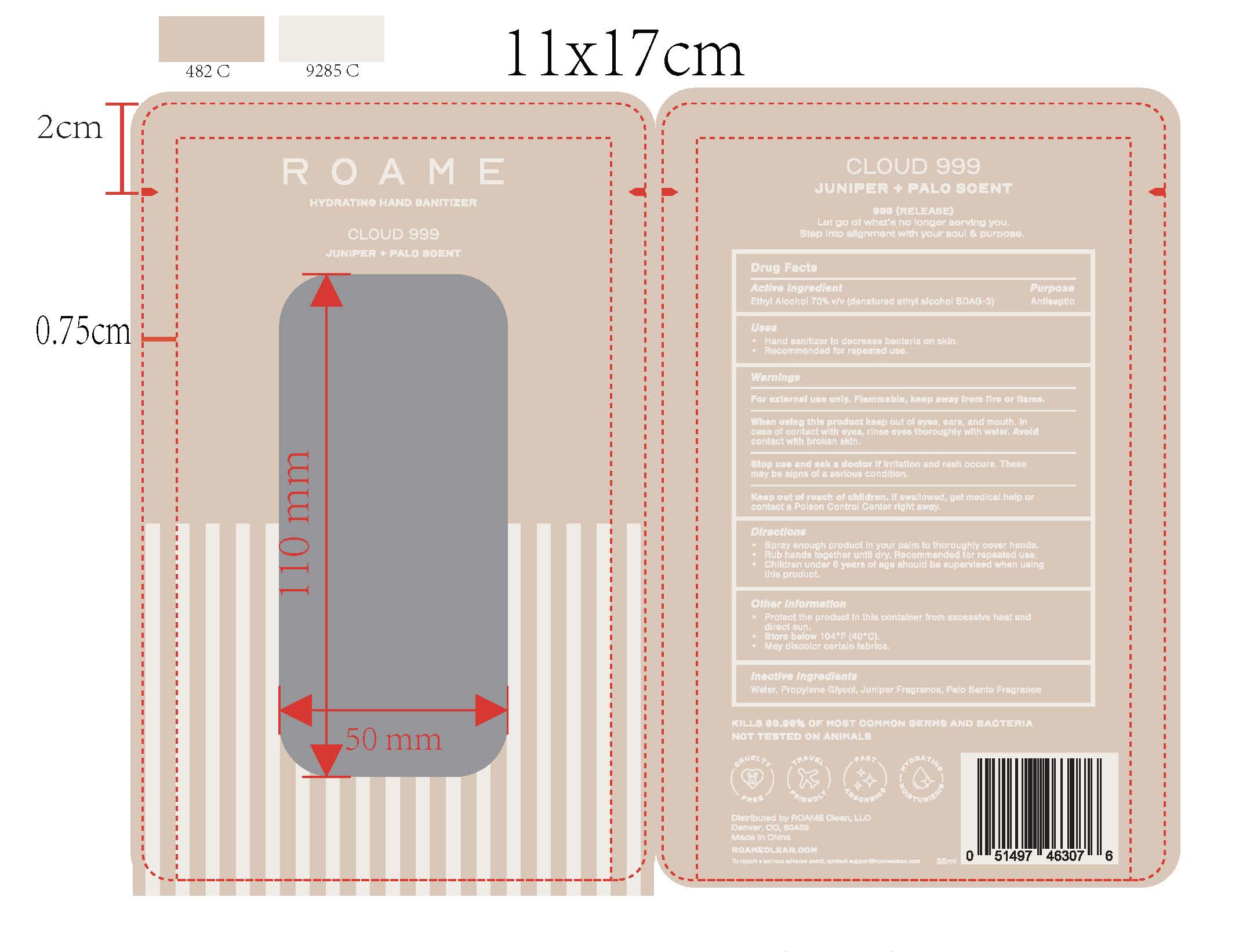 DRUG LABEL: ROAME Moisturizing Hand Sanitizer Cloud 999
NDC: 85154-100 | Form: SPRAY
Manufacturer: Roame LLC
Category: otc | Type: HUMAN OTC DRUG LABEL
Date: 20250114

ACTIVE INGREDIENTS: ALCOHOL 70 mL/100 mL
INACTIVE INGREDIENTS: WATER; PROPYLENE GLYCOL

ROAME Moisturizing Hand Sanitizer Cloud 999

Active ingredients

Ethyl Alcohol (denatured ethyl alcohol SDAG-3) 70%

Purpose

Hand Sanitizer

Uses

Hand Sanitizer

Warnings

For external use only. Flammable, keep away from fire or flame.

When using this product

keep out of eyes, ears, and mouth. In case of contact with eyes, rinse eyes thoroughly with water. Avoid contact with broken skin.

Stop use and ask a doctor if

irritation and rash occurs. These may be signs of a serious condition.

Keep out of reach of children.

If swallowed, get medical help or contact a Poison Control Center right away.

Directions

-Spray enough product in your palm to thoroughly cover hands.
-Rub hands together until dry. Recommend for repeated use.
-Children under 6 years of age should be supervised when using this product.

Other information

-Protect the product in this container from excessive heat and direct sun.
-Store below 104 degrees F (40 degrees C)
-May discolor certain fabrics.

Inactive ingredients

Water, propylene glycol, juniper fragrance, palo santo fragrance